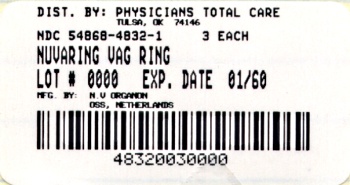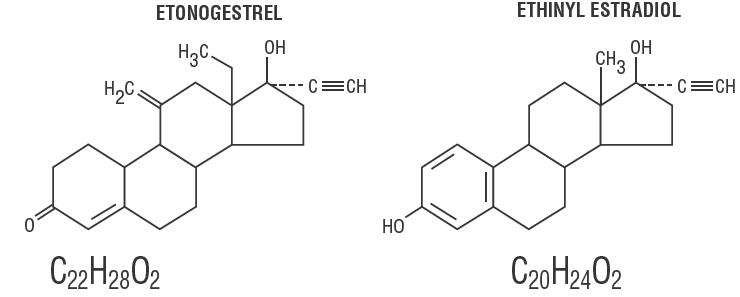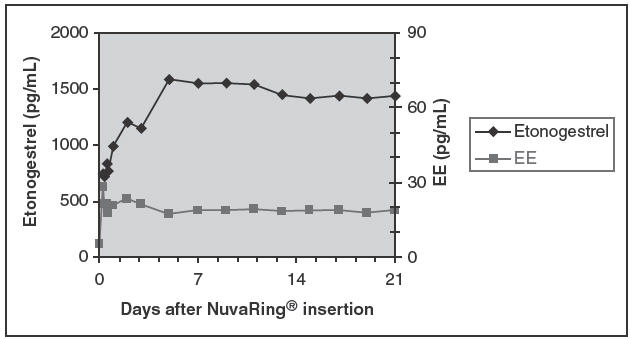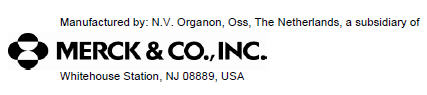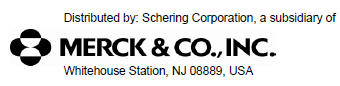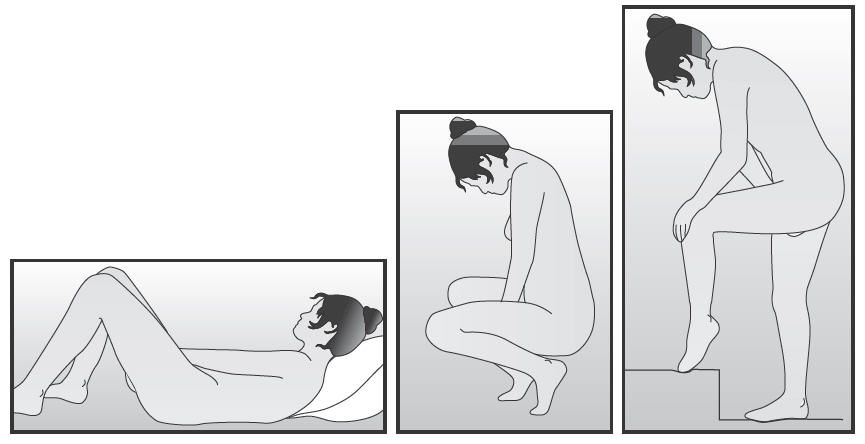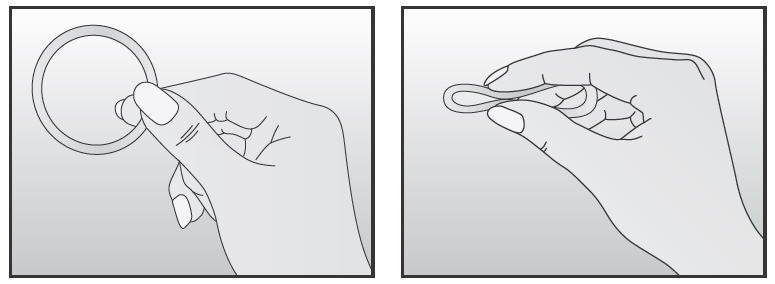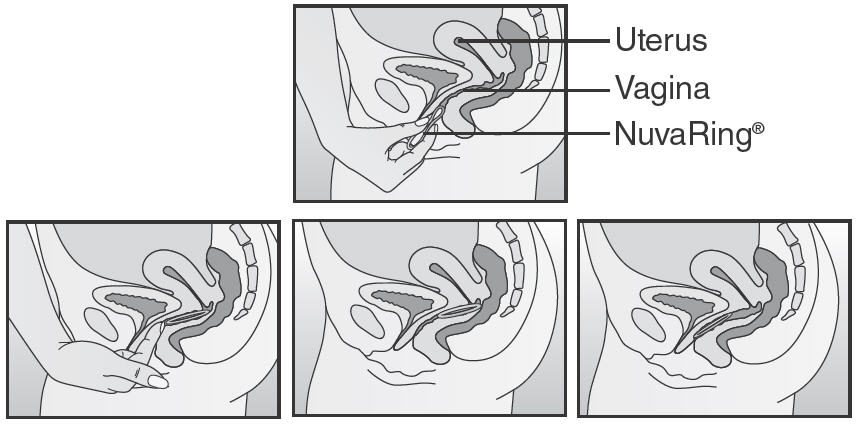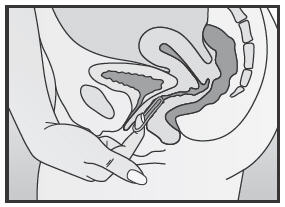 DRUG LABEL: NuvaRing
NDC: 54868-4832 | Form: INSERT, EXTENDED RELEASE
Manufacturer: Physicians Total Care, Inc.
Category: prescription | Type: HUMAN PRESCRIPTION DRUG LABEL
Date: 20120209

ACTIVE INGREDIENTS: etonogestrel 11.7 mg/1 1; ethinyl estradiol 2.7 mg/1 1
INACTIVE INGREDIENTS: ethylene-vinyl acetate copolymer (28% vinyl acetate); ethylene-vinyl acetate copolymer (9% vinylacetate); magnesium stearate

NUVARING®
(etonogestrel/ethinyl estradiol vaginal ring)

delivers 0.120 mg/0.015 mg per day

Women should be counseled that this product does not protect against HIV infection (AIDS) and other sexually transmitted diseases.

FOR VAGINAL USE ONLY

DESCRIPTION

NuvaRing® (etonogestrel/ethinyl estradiol vaginal ring) is a non-biodegradable, flexible, transparent, colorless to almost colorless, combination contraceptive vaginal ring containing two active components, a progestin, etonogestrel (13-ethyl-17-hydroxy-11-methylene-18,19-dinor-17α-pregn-4-en-20-yn-3-one) and an estrogen, ethinyl estradiol (19-nor-17α-pregna-1,3,5(10)-trien-20-yne-3, 17-diol).When placed in the vagina, each ring releases on average 0.120 mg/day of etonogestrel and 0.015 mg/day of ethinyl estradiol over a three-week period of use. NuvaRing® is made of ethylene vinylacetate copolymers (28% and 9% vinylacetate) and magnesium stearate and contains 11.7 mg etonogestrel and 2.7 mg ethinyl estradiol. NuvaRing® is latex-free. NuvaRing® has an outer diameter of 54 mm and a cross-sectional diameter of 4 mm. The molecular weights for etonogestrel and ethinyl estradiol are 324.46 and 296.40, respectively.

The structural formulas are as follows:

CLINICAL PHARMACOLOGY

Combination hormonal contraceptives act by suppression of gonadotropins. Although the primary effect of this action is inhibition of ovulation, other alterations include changes in the cervical mucus (which increase the difficulty of sperm entry into the uterus) and the endometrium (which reduce the likelihood of implantation).

Receptor binding studies, as well as studies in animals, have shown that etonogestrel, the biologically active metabolite of desogestrel, combines high progestational activity with low intrinsic androgenicity. The relevance of this latter finding in humans is unknown.

Pharmacokinetics

Absorption

Etonogestrel

Etonogestrel released by NuvaRing® is rapidly absorbed. The bioavailability of etonogestrel after vaginal administration is approximately 100%. The serum etonogestrel and ethinyl estradiol concentrations observed during three weeks of NuvaRing® use are summarized in Table I.

Ethinyl estradiol

Ethinyl estradiol released by NuvaRing® is rapidly absorbed. The bioavailability of ethinyl estradiol after vaginal administration is approximately 56%, which is comparable to that with oral administration of ethinyl estradiol. The serum ethinyl estradiol concentrations observed during three weeks of NuvaRing® use are summarized in Table I.

TABLE I: MEAN (SD) SERUM ETONOGESTREL AND ETHINYL ESTRADIOL CONCENTRATIONS (n=16).
 | 1 week | 2 weeks | 3 weeks
etonogestrel (pg/mL) | 1578 (408) | 1476 (362) | 1374 (328)
ethinyl estradiol (pg/mL) | 19.1 (4.5) | 18.3 (4.3) | 17.6 (4.3)

The pharmacokinetic profile of etonogestrel and ethinyl estradiol during use of NuvaRing® is shown in Figure 1.

Figure 1. Mean serum concentration-time profile of etonogestrel and ethinyl estradiol during three weeks of NuvaRing® use.

The pharmacokinetic parameters of etonogestrel and ethinyl estradiol were determined during one cycle of NuvaRing® use in 16 healthy female subjects and are summarized in Table II.

TABLE II: MEAN (SD) PHARMACOKINETIC PARAMETERS OF NuvaRing® (n=16).
Hormone | Cmax pg/mL | Tmax hr | t1/2 hr | CL L/hr
etonogestrel | 1716 (445) | 200.3 (69.6) | 29.3 (6.1) | 3.4 (0.8)
ethinyl estradiol | 34.7 (17.5) | 59.3 (67.5) | 44.7 (28.8) | 34.8 (11.6)
Cmax- maximum serum drug concentration
Tmax- time at which maximum serum drug concentration occurs
t1/2 - elimination half-life, calculated by 0.693/Kelim
CL - apparent clearance

Distribution

Etonogestrel

Etonogestrel is approximately 32% bound to sex hormone-binding globulin (SHBG) and approximately 66% bound to albumin in blood.

Ethinyl estradiol

Ethinyl estradiol is highly but not specifically bound to serum albumin (98.5%) and induces an increase in the serum concentrations of SHBG.

Metabolism

In vitro data shows that both etonogestrel and ethinyl estradiol are metabolized in liver microsomes by the cytochrome P450 3A4 isoenzyme. Ethinyl estradiol is primarily metabolized by aromatic hydroxylation, but a wide variety of hydroxylated and methylated metabolites are formed. These are present as free metabolites and as sulfate and glucuronide conjugates. The hydroxylated ethinyl estradiol metabolites have weak estrogenic activity. The biological activity of etonogestrel metabolites is unknown.

Excretion

Etonogestrel and ethinyl estradiol are primarily eliminated in urine, bile and feces.

Special Populations

Race

No formal studies were conducted to evaluate the effect of race on the pharmacokinetics of NuvaRing®.

Hepatic Insufficiency

No formal studies were conducted to evaluate the effect of hepatic disease on the pharmacokinetics, safety, and efficacy of NuvaRing®. However, steroid hormones may be poorly metabolized in women with impaired liver function (see PRECAUTIONS).

Renal Insufficiency

No formal studies were conducted to evaluate the effect of renal disease on the pharmacokinetics, safety, and efficacy of NuvaRing®.

Drug-Drug Interactions

Interactions between contraceptive steroids and other drugs have been reported in the literature (see PRECAUTIONS). The drug interactions of NuvaRing® were evaluated in several studies.

A single-dose vaginal administration of an oil-based 1200 mg miconazole nitrate capsule increased the serum concentrations of etonogestrel and ethinyl estradiol by approximately 17% and 16%, respectively. Following multiple doses of 200 mg miconazole nitrate by vaginal suppository or vaginal cream, the mean serum concentrations of etonogestrel and ethinyl estradiol increased by up to 40%.

A single-dose vaginal administration of 100 mg water-based nonoxynol-9 spermicide gel did not affect the serum concentrations of etonogestrel or ethinyl estradiol.

The serum concentrations of etonogestrel and ethinyl estradiol were not affected by concomitant administration of oral amoxicillin or doxycycline in standard dosages during 10 days of antibiotic treatment.

Tampon Use

The use of tampons had no effect on serum concentrations of etonogestrel and ethinyl estradiol during use of NuvaRing®.

INDICATIONS AND USAGE

NuvaRing® is indicated for the prevention of pregnancy in women who elect to use this product as a method of contraception. Like oral contraceptives, NuvaRing® is highly effective if used as recommended in this label.

In three large clinical trials of 13 cycles of NuvaRing® use, pregnancy rates were between one and two per 100 women-years of use. Table III lists the pregnancy rates for users of various contraceptive methods.

TABLE III: PERCENTAGE OF WOMEN EXPERIENCING AN UNINTENDED PREGNANCY DURING THE FIRST YEAR OF TYPICAL USE AND THE FIRST YEAR OF PERFECT USE OF CONTRACEPTION AND THE PERCENTAGE CONTINUING USE AT THE END OF THE FIRST YEAR: UNITED STATES.
 | % of Women Experiencing an Unintended Pregnancy within the First Year of Use |  | % of Women Continuing Use at One Year [Among couples attempting to avoid pregnancy, the percentage who continue to use a method for one year.]
Method | Typical Use [Among typical couples who initiate use of a method (not necessarily for the first time), the percentage who experience an accidental pregnancy during the first year if they do not stop use for any other reason.] | Perfect Use [Among couples who initiate use of a method (not necessarily for the first time) and who use it perfectly (both consistently and correctly), the percentage who experience an accidental pregnancy during the first year if they do not stop use for any other reason.] | % of Women Continuing Use at One Year [Among couples attempting to avoid pregnancy, the percentage who continue to use a method for one year.]
(1) | (2) | (3) | (4)
Chance [The percents becoming pregnant in columns (2) and (3) are based on data from populations where contraception is not used and from women who cease using contraception in order to become pregnant. Among such populations, about 89% become pregnant within one year. This estimate was lowered slightly (to 85%) to represent the percent who would become pregnant within one year among women now relying on reversible methods of contraception if they abandoned contraception altogether.] | 85 | 85
Spermicides [Foams, creams, gels, vaginal suppositories, and vaginal film.] | 26 | 6 | 40
Periodic abstinence | 25 |  | 63
Calendar |  | 9
Ovulation Method |  | 3
Sympto-Thermal [Cervical mucus (ovulation) method supplemented by calendar in the pre-ovulatory and basal body temperature in the post-ovulatory phases.] |  | 2
Post-Ovulation |  | 1
Cap [With spermicidal cream or jelly.]
Parous Women | 40 | 26 | 42
Nulliparous Women | 20 | 9 | 56
Sponge
Parous Women | 40 | 20 | 42
Nulliparous Women | 20 | 9 | 56
Diaphragm | 20 | 6 | 56
Withdrawal | 19 | 4
Condom [Without spermicides.]
Female (Reality) | 21 | 5 | 56
Male | 14 | 3 | 61
Pill | 5 |  | 71
Progestin Only |  | 0.5
Combined |  | 0.1
IUD
Progesterone T | 2.0 | 1.5 | 81
Copper T 380A | 0.8 | 0.6 | 78
LNg 20 | 0.1 | 0.1 | 81
Depo-Provera | 0.3 | 0.3 | 70
Norplant and Norplant-2 | 0.05 | 0.05 | 88
Female sterilization | 0.5 | 0.5 | 100
Male sterilization | 0.15 | 0.10 | 100
Emergency Contraceptive Pills: Treatment initiated within 72 hours after unprotected intercourse reduces the risk of pregnancy by at least 75%. [The treatment schedule is one dose within 72 hours after unprotected intercourse, and a second dose 12 hours after the first dose. The FDA has declared the following brands of oral contraceptives to be safe and effective for emergency contraception: Ovral (one dose is two white pills), Alesse (one dose is five pink pills), Nordette or Levlen (one dose is four yellow pills).]
Lactation Amenorrhea Method: LAM is a highly effective, temporary method of contraception. [However, to maintain effective protection against pregnancy, another method of contraception must be used as soon as menstruation resumes, the frequency or duration of breast-feeds is reduced, bottle feeds are introduced, or the baby reaches six months of age.]
Adapted from Hatcher et al., Contraceptive Technology, 17th Revised Edition. New York, NY: Irvington Publishers, 1998.

CONTRAINDICATIONS

NuvaRing® should not be used in women who currently have the following conditions:

- Thrombophlebitis or thromboembolic disorders
- A past history of deep vein thrombophlebitis or thromboembolic disorders
- Cerebral vascular or coronary artery disease (current or history)
- Valvular heart disease with thrombogenic complications
- Severe hypertension
- Diabetes with vascular involvement
- Headaches with focal neurological symptoms
- Major surgery with prolonged immobilization
- Known or suspected carcinoma of the breast or personal history of breast cancer
- Carcinoma of the endometrium or other known or suspected estrogen-dependent neoplasia
- Undiagnosed abnormal genital bleeding
- Cholestatic jaundice of pregnancy or jaundice with prior hormonal contraceptive use
- Hepatic tumors (benign or malignant) or active liver disease
- Known or suspected pregnancy
- Heavy smoking (≥15 cigarettes per day) and over age 35
- Hypersensitivity to any of the components of NuvaRing®

WARNINGS

BOXED WARNING

Cigarette smoking increases the risk of serious cardiovascular side effects from combination oral contraceptive use. This risk increases with age and with heavy smoking (15 or more cigarettes per day) and is quite marked in women over 35 years of age. Women who use combination hormonal contraceptives, including NuvaRing®, should be strongly advised not to smoke.

NuvaRing® and other contraceptives that contain both an estrogen and a progestin are called combination hormonal contraceptives. There is no epidemiologic data available to determine whether safety and efficacy with the vaginal route of administration of combination hormonal contraceptives would be different than the oral route.

The use of oral contraceptives is associated with increased risks of several serious conditions including venous and arterial thrombotic and thromboembolic events (such as myocardial infarction, thromboembolism, and stroke), hepatic neoplasia, gallbladder disease, and hypertension, although the risk of serious morbidity or mortality is very small in healthy women without underlying risk factors. The risk of morbidity and mortality increases significantly in the presence of other underlying risk factors such as certain inherited thrombophilias, hypertension, hyperlipidemias, obesity, and diabetes.

The information contained in this package insert is principally based on studies carried out in women who used oral contraceptives with formulations of higher doses of estrogens and progestogens than those in common use today. The effect of long-term use of oral contraceptives with lower doses of both estrogens and progestogens remains to be determined.

Throughout this labeling, epidemiologic studies reported are of two types: retrospective or case control studies and prospective or cohort studies. Case control studies provide a measure of the relative risk of a disease, namely, a ratio of the incidence of a disease among oral contraceptive users to that among non-users. The relative risk does not provide information on the actual clinical occurrence of a disease. Cohort studies provide a measure of attributable risk, which is the difference in the incidence of disease between oral contraceptive users and non-users. The attributable risk does provide information about the actual occurrence of a disease in the population. For further information, the reader is referred to a text on epidemiologic methods.

1. THROMBOEMBOLIC DISORDERS AND OTHER VASCULAR PROBLEMS

a. Thromboembolism

An increased risk of thromboembolic and thrombotic disease associated with the use of oral contraceptives is well established. Case control studies have found the relative risk of users compared to non-users to be three for the first episode of superficial venous thrombosis, four to 11 for deep vein thrombosis or pulmonary embolism, and 1.5 to six for women with predisposing conditions for venous thromboembolic disease. Cohort studies have shown the relative risk to be somewhat lower, about three for new cases and about 4.5 for new cases requiring hospitalization. The risk of thromboembolic disease associated with oral contraceptives is not related to length of use and disappears after pill use is stopped.

Several epidemiology studies indicate that third generation oral contraceptives, including those containing desogestrel (etonogestrel, the progestin in NuvaRing®, is the biologically active metabolite of desogestrel), are associated with a higher risk of venous thromboembolism than certain second generation oral contraceptives. In general, these studies indicate an approximate two-fold increased risk, which corresponds to an additional one to two cases of venous thromboembolism per 10,000 women-years of use. However, data from additional studies have not shown this two-fold increase in risk. It is unknown if NuvaRing® has a different risk of venous thromboembolism than second generation oral contraceptives.

A two- to four-fold increase in relative risk of post-operative thromboembolic complications has been reported with the use of oral contraceptives. The relative risk of venous thrombosis in women who have predisposing conditions is twice that of women without such medical conditions. If feasible, combination hormonal contraceptives, including NuvaRing®, should be discontinued at least four weeks prior to and for two weeks after elective surgery of a type associated with an increase in risk of thromboembolism and during and following prolonged immobilization. Since the immediate postpartum period is also associated with an increased risk of thromboembolism, combination hormonal contraceptives, such as NuvaRing®, should be started no earlier than four to six weeks after delivery in women who elect not to breast-feed.

The clinician should be alert to the earliest manifestations of thrombotic disorders (thrombophlebitis, pulmonary embolism, cerebrovascular disorders, and retinal thrombosis). Should any of these occur or be suspected, NuvaRing® should be discontinued immediately.

b. Myocardial infarction

An increased risk of myocardial infarction has been attributed to oral contraceptive use. This risk is primarily in smokers or women with other underlying risk factors for coronary artery disease such as hypertension, hypercholesterolemia, morbid obesity, and diabetes. The relative risk of heart attack for current combination oral contraceptive users has been estimated to be two to six. The risk is very low in women under the age of 30.

Smoking in combination with oral contraceptive use has been shown to contribute substantially to the incidence of myocardial infarction in women in their mid-thirties or older with smoking accounting for the majority of excess cases. Mortality rates associated with circulatory disease have been shown to increase substantially in smokers, over the age of 35 and non-smokers over the age of 40 among women who use oral contraceptives (see Table IV).

TABLE IV: CIRCULATORY DISEASE MORTALITY RATES PER 100,000 WOMAN-YEARS BY AGE, SMOKING STATUS, AND COMBINATION ORAL CONTRACEPTIVE USE.
AGE | EVER-USERS NON-SMOKERS | EVER-USERS SMOKERS | CONTROLS NON-SMOKERS | CONTROLS SMOKERS
15–24 | 0.0 | 10.5 | 0.0 | 0.0
25–34 | 4.4 | 14.2 | 2.7 | 4.2
35–44 | 21.5 | 63.4 | 6.4 | 15.2
45+ | 52.4 | 206.7 | 11.4 | 27.9
(Adapted from P.M. Layde and V. Beral, Lancet, 1981;1:541–546.)

Oral contraceptives may compound the effects of well-known risk factors, such as hypertension, diabetes, hyperlipidemias, age, and obesity. In particular, some progestogens are known to decrease HDL cholesterol and cause glucose intolerance, while estrogens may create a state of hyperinsulinism. Oral contraceptives have been shown to increase blood pressure among users (see WARNINGS). Similar effects on risk factors have been associated with an increased risk of heart disease. NuvaRing® must be used with caution in women with cardiovascular disease risk factors.

c. Cerebrovascular diseases

Oral contraceptives have been shown to increase both the relative and attributable risks of cerebrovascular events (thrombotic and hemorrhagic strokes), although, in general, the risk is greatest among older (>35 years), hypertensive women who also smoke. Hypertension was found to be a risk factor for both users and non-users, for both types of strokes, while smoking interacted to increase the risk for hemorrhagic strokes.

In a large study, the relative risk of thrombotic strokes has been shown to range from three for normotensive users to 14 for users with severe hypertension. The relative risk of hemorrhagic stroke is reported to be 1.2 for non-smokers who used oral contraceptives, 2.6 for smokers who did not use oral contraceptives, 7.6 for smokers who used oral contraceptives, 1.8 for normotensive users and 25.7 for users with severe hypertension. The attributable risk is also greater in older women. Oral contraceptives also increase the risk for stroke in women with other underlying risk factors such as certain inherited or acquired thrombophilias, hyperlipidemias, and obesity. Women with migraine (particularly migraine with aura) who take combination oral contraceptives may be at an increased risk of stroke.

d. Dose-related risk of vascular disease from oral contraceptives

A positive association has been observed between the amount of estrogen and progestogen in oral contraceptives and the risk of vascular disease. A decline in serum high-density lipoproteins (HDL) has been reported with many progestational agents. A decline in serum high-density lipoproteins has been associated with an increased incidence of ischemic heart disease. Because estrogens increase HDL cholesterol, the net effect of an oral contraceptive depends on a balance achieved between doses of estrogen and progestogen and the nature and absolute amount of progestogens used in the contraceptives. The activity and amount of both hormones should be considered in the choice of a hormonal contraceptive.

Minimizing exposure to estrogen and progestogen is in keeping with good principles of therapeutics. For any particular estrogen/progestogen combination, the dosage regimen prescribed should be one which contains the least amount of estrogen and progestogen that is compatible with a low failure rate and the needs of the individual patient. New acceptors of hormonal contraceptive agents should be started on a product containing the lowest hormone content that provides satisfactory results in the individual.

e. Persistence of risk of vascular disease

There are two studies that have shown persistence of risk of vascular disease for ever-users of oral contraceptives. In a study in the United States, the risk of developing myocardial infarction after discontinuing oral contraceptives persists for at least nine years for women 40–49 years old who had used oral contraceptives for five or more years, but this increased risk was not demonstrated in other age groups. In another study in Great Britain, the risk of developing cerebrovascular disease persisted for at least six years after discontinuation of oral contraceptives, although excess risk was very small. However, both studies were performed with oral contraceptive formulations containing 50 micrograms or more of estrogen.

It is unknown whether NuvaRing® is distinct from combination oral contraceptives with regard to the occurrence of venous or arterial thrombosis.

2. ESTIMATES OF MORTALITY FROM CONTRACEPTIVE USE

One study gathered data from a variety of sources that have estimated the mortality rate associated with different methods of contraception at different ages (Table V). These estimates include the combined risk of death associated with contraceptive methods plus the risk attributable to pregnancy in the event of method failure. Each method of contraception has its specific benefits and risks. The study concluded that with the exception of oral contraceptive users age 35 and older who smoke and age 40 and older who do not smoke, mortality associated with all methods of birth control is low and below that associated with childbirth.

The observation of a possible increase in risk of mortality with age for oral contraceptive users is based on data gathered in the 1970's, but not reported until 1983. However, current clinical practice involves the use of lower estrogen-dose formulations combined with careful restriction of hormonal contraceptive use to women who do not have the various risk factors listed in this labeling.

Because of these changes in practice and, also, because of some limited new data which suggest that the risk of cardiovascular disease with the use of oral contraceptives may now be less than previously observed, the Fertility and Maternal Health Drugs Advisory Committee was asked to review the topic in 1989. The Committee concluded that although cardiovascular disease risks may be increased with oral contraceptive use after age 40 in healthy non-smoking women (even with the newer low-dose formulations), there are also greater potential health risks associated with pregnancy in older women and with the alternative surgical and medical procedures which may be necessary if such women do not have access to effective and acceptable means of contraception. Therefore, the Committee recommended that the benefits of low-dose hormonal oral contraceptive use by healthy non-smoking women over 40 may outweigh the possible risks. Older women, as all women who take hormonal contraceptives, should take the lowest possible dose formulation that is effective and meets the individual patient needs.

TABLE V: ANNUAL NUMBER OF BIRTH-RELATED OR METHOD-RELATED DEATHS ASSOCIATED WITH CONTROL OF FERTILITY PER 100,000 NON-STERILE WOMEN, BY FERTILITY CONTROL METHOD ACCORDING TO AGE.
Method of control and outcome | 15–19 | 20–24 | 25–29 | 30–34 | 35–39 | 40–44
No fertility control methods [Deaths are birth related] | 7.0 | 7.4 | 9.1 | 14.8 | 25.7 | 28.2
Oral contraceptives non-smoker [Deaths are method related] | 0.3 | 0.5 | 0.9 | 1.9 | 13.8 | 31.6
Oral contraceptives smoker | 2.2 | 3.4 | 6.6 | 13.5 | 51.1 | 117.2
IUD | 0.8 | 0.8 | 1.0 | 1.0 | 1.4 | 1.4
Condom | 1.1 | 1.6 | 0.7 | 0.2 | 0.3 | 0.4
Diaphragm/spermicide | 1.9 | 1.2 | 1.2 | 1.3 | 2.2 | 2.8
Periodic abstinence | 2.5 | 1.6 | 1.6 | 1.7 | 2.9 | 3.6
(Adapted from H.W. Ory, Family Planning Perspectives 1983;15:50–56.)

3. CARCINOMA OF THE REPRODUCTIVE ORGANS AND BREASTS

Numerous epidemiologic studies have been performed on the incidence of breast, endometrial, ovarian, and cervical cancer in women using combination oral contraceptives. Although the risk of breast cancer may be slightly increased among current users of oral contraceptives (RR = 1.24), this excess risk decreases over time after oral contraceptive discontinuation and by 10 years after cessation the increased risk disappears. The risk does not increase with duration of use, and no relationships have been found with dose or type of steroid. The patterns of risk are also similar regardless of a woman's reproductive history or her family breast cancer history. The subgroup for whom risk has been found to be significantly elevated is women who first used oral contraceptives before age 20, but because breast cancer is so rare at these young ages, the number of cases attributable to this early oral contraceptive use is extremely small. Breast cancers diagnosed in current or previous oral contraceptive users tend to be less advanced clinically than in never-users. Women who currently have or have had breast cancer should not use hormonal contraceptives because breast cancer is a hormone-sensitive tumor.

Some studies suggest that combination oral contraceptive use has been associated with an increase in the risk of cervical intraepithelial neoplasia in some populations of women. However, there continues to be controversy about the extent to which such findings may be due to differences in sexual behavior and other factors.

In spite of many studies of the relationship between oral contraceptive use and breast and cervical cancers, a cause-and-effect relationship has not been established.

It is unknown whether NuvaRing® is distinct from oral contraceptives with regard to the above statements.

4. HEPATIC NEOPLASIA

Benign hepatic adenomas are associated with oral contraceptive use, although the incidence of benign tumors is rare in the United States. Indirect calculations have estimated the attributable risk to be in the range of 3.3 cases per 100,000 for users, a risk that increases after four or more years of use. Rupture of rare, benign, hepatic adenomas may cause death through intra-abdominal hemorrhage.

Studies from Britain have shown an increased risk of developing hepatocellular carcinoma in long term (>8 years) oral contraceptive users. However, these cancers are extremely rare in the US and the attributable risk (the excess incidence) of liver cancers in oral contraceptive users approaches less than one per million users. It is unknown whether NuvaRing® is distinct from oral contraceptives in this regard.

5. OCULAR LESIONS

There have been clinical case reports of retinal thrombosis associated with the use of oral contraceptives. NuvaRing® should be discontinued if there is unexplained partial or complete loss of vision, onset of proptosis or diplopia, papilledema, or retinal vascular lesions. Appropriate diagnostic and therapeutic measures should be undertaken immediately.

6. HORMONAL CONTRACEPTIVE USE BEFORE OR DURING EARLY PREGNANCY

Hormonal contraceptives should not be used during pregnancy.

Extensive epidemiologic studies have revealed no increased risk of birth defects in women who have used oral contraceptives prior to pregnancy. Studies also do not suggest a teratogenic effect, particularly in so far as cardiac anomalies and limb reduction defects are concerned, when oral contraceptives are taken inadvertently during early pregnancy.

Combination hormonal contraceptives, such as NuvaRing®, should not be used to induce withdrawal bleeding as a test for pregnancy. NuvaRing® should not be used during pregnancy to treat threatened or habitual abortion. It is recommended that for any woman who has not adhered to the prescribed regimen for use of NuvaRing® and has missed a menstrual period or who has missed two consecutive periods, pregnancy should be ruled out.

7. GALLBLADDER DISEASE

Combination hormonal contraceptives, such as NuvaRing®, may worsen existing gallbladder disease and may accelerate the development of this disease in previously asymptomatic women. Women with a history of combination hormonal contraceptive-related cholestasis are more likely to have the condition recur with subsequent combination hormonal contraceptive use.

8. CARBOHYDRATE AND LIPID METABOLIC EFFECTS

Hormonal contraceptives have been shown to cause a decrease in glucose tolerance in some users. However, in the non-diabetic woman, combination hormonal contraceptives appear to have no effect on fasting blood glucose. Prediabetic and diabetic women should be carefully observed while taking combination hormonal contraceptives, such as NuvaRing®. In a clinical study involving 37 NuvaRing®-treated subjects, glucose tolerance tests showed no clinically significant changes in serum glucose levels from baseline to cycle six.

A small proportion of women will have persistent hypertriglyceridemia while using oral contraceptives. Changes in serum triglycerides and lipoprotein levels have been reported in combination hormonal contraceptive users.

9. ELEVATED BLOOD PRESSURE

Women with severe hypertension should not be started on hormonal contraceptives. An increase in blood pressure has been reported in women taking oral contraceptives and this increase is more likely in older oral contraceptive users and with continued use. Data from the Royal College of General Practitioners and subsequent randomized trials have shown that the incidence of hypertension increases with increasing concentrations of progestogens.

Women with a history of hypertension or hypertension-related diseases, or renal disease should be encouraged to use another method of contraception. If these women elect to use NuvaRing®, they should be monitored closely and if significant elevation of blood pressure occurs, NuvaRing® should be discontinued. For most women, elevated blood pressure will return to normal after stopping hormonal contraceptives, and there is no difference in the occurrence of hypertension between former and never-users.

10. HEADACHE

The onset or exacerbation of migraine or development of headache with a new pattern which is recurrent, persistent, or severe requires discontinuation of NuvaRing® and evaluation of the cause.

11. BLEEDING IRREGULARITIES

Bleeding Patterns

Breakthrough bleeding and spotting are sometimes encountered in women using NuvaRing®. If abnormal bleeding while using NuvaRing® persists or is severe, appropriate investigation should be instituted to rule out the possibility of organic pathology or pregnancy, and appropriate treatment should be instituted when necessary. In the event of amenorrhea, pregnancy should be ruled out.

Bleeding patterns were evaluated in three large clinical studies. In the US-Canadian study (n=1177), the percentages of subjects with breakthrough bleeding/spotting ranged from 7.2 to 11.7% during cycles 1–13. In the two non-US studies, the percentages of subjects with breakthrough bleeding/spotting ranged from 2.6 to 6.4% (Study 1, n=1145 European and Israeli subjects) and from 2.0 to 8.7% (Study 2, n=512 European and South American subjects). In these three studies, the percentages of women who did not have withdrawal bleeding in a given cycle ranged from 0.3 to 3.8%.

Some women may encounter amenorrhea or oligomenorrhea after discontinuing use of NuvaRing®, especially when such a condition was pre-existent.

12. ECTOPIC PREGNANCY

Ectopic as well as intrauterine pregnancy may occur in contraceptive failures.

PRECAUTIONS

1. SEXUALLY TRANSMITTED DISEASES

Women should be counseled that this product does not protect against HIV infection (AIDS) and other sexually transmitted diseases.

2. PHYSICAL EXAMINATION AND FOLLOW-UP

It is routine medical practice for women using NuvaRing®, as for all women, to have an annual medical evaluation including physical examination and relevant laboratory tests. The physical examination should include special reference to blood pressure, breasts, abdomen, pelvic organs and vagina (including cervical cytology). In case of undiagnosed, persistent or recurrent abnormal vaginal bleeding, appropriate measures should be conducted to rule out malignancy. Women with a family history of breast cancer or who have breast nodules should be monitored with particular care.

3. LIPID DISORDERS

Women who are being treated for hyperlipidemias should be followed closely if they elect to use NuvaRing®. Some progestogens may elevate LDL levels and may render the control of hyperlipidemias more difficult.

In women with familial defects of lipoprotein metabolism receiving estrogen-containing preparations, there have been case reports of significant elevations of plasma triglycerides leading to pancreatitis.

4. LIVER FUNCTION

If jaundice develops in any woman using NuvaRing®, product use should be discontinued. The hormones in NuvaRing® may be poorly metabolized in women with impaired liver function.

5. FLUID RETENTION

Steroid hormones like those in NuvaRing®, may cause some degree of fluid retention. NuvaRing® should be prescribed with caution, and only with careful monitoring, in women with conditions which might be aggravated by fluid retention.

6. EMOTIONAL DISORDERS

Women becoming significantly depressed while taking hormonal contraceptives should stop the medication and use an alternate method of contraception in an attempt to determine whether the symptom is drug related. Women with a history of depression should be carefully observed and the drug discontinued if depression recurs to a serious degree.

7. TAMPON USE

On rare occasions, NuvaRing® may be expelled while removing a tampon (see EXPULSION). Pharmacokinetic data show that the use of tampons has no effect on the systemic absorption of the hormones released by NuvaRing®.

8. TOXIC SHOCK SYNDROME (TSS)

Cases of toxic shock syndrome have been associated with tampons and certain barrier contraceptives. Very rare cases of TSS have been reported by NuvaRing® users; in some cases the women were also using tampons. No causal relationship between the use of NuvaRing® and TSS has been established. If a patient exhibits signs or symptoms of TSS, the possibility of this diagnosis should not be excluded and appropriate medical evaluation and treatment initiated.

9. CONTACT LENSES

Contact lens wearers who develop visual changes or changes in lens tolerance should be assessed by an ophthalmologist.

10. DRUG INTERACTIONS

Changes in contraceptive effectiveness associated with co-administration of other drugs:

a. Anti-infective agents and anticonvulsants

Contraceptive effectiveness may be reduced when hormonal contraceptives are co-administered with some antifungals, anticonvulsants, and other drugs that increase metabolism of contraceptive steroids. This could result in unintended pregnancy or breakthrough bleeding. Examples include barbiturates, griseofulvin, rifampin, phenylbutazone, phenytoin, carbamazepine, felbamate, oxcarbazepine, topiramate, and modafinil. Women may need to use an additional contraceptive method when taking such medications.

b. Anti-HIV protease inhibitors

Several of the anti-HIV protease inhibitors have been studied with co-administration of oral combination hormonal contraceptives; significant changes (increases and decreases) in the plasma levels of the estrogen and progestin have been noted in some cases. The efficacy and safety of hormonal contraceptive products may be affected with co-administration of anti-HIV protease inhibitors. Healthcare providers should refer to the label of the individual anti-HIV protease inhibitors for further drug-drug interaction information.

c. Herbal products

Herbal products containing St. John's Wort (hypericum perforatum) may induce hepatic enzymes (cytochrome P450) and p-glycoprotein transporter and may reduce the effectiveness of contraceptive steroids. This may also result in breakthrough bleeding.

Increase in plasma hormone levels associated with co-administered drugs

Co-administration of atorvastatin and certain oral contraceptives containing ethinyl estradiol increase AUC values for ethinyl estradiol by approximately 20%. Ascorbic acid and acetaminophen may increase plasma ethinyl estradiol levels, possibly by inhibition of conjugation. CYP 3A4 inhibitors such as itraconazole or ketoconazole may increase plasma hormone levels. Co-administration of vaginal miconazole nitrate and NuvaRing® increases the serum concentrations of etonogestrel and ethinyl estradiol by up to 40%.

Changes in plasma levels of co-administered drugs

Combination hormonal contraceptives containing some synthetic estrogens (e.g., ethinyl estradiol) may inhibit the metabolism of other compounds. Increased plasma concentrations of cyclosporine, prednisolone, and theophylline have been reported with concomitant administration of oral contraceptives. In addition, oral contraceptives may induce the conjugation of other compounds. Decreased plasma concentrations of acetaminophen and increased clearance of temazepam, salicylic acid, morphine and clofibric acid have been noted when these drugs were administered with oral contraceptives.

11. INTERACTIONS WITH LABORATORY TESTS

Certain endocrine and liver function tests and blood components may be affected by combined hormonal contraceptives:

1. Increased prothrombin and factors VII, VIII, IX and X; decreased antithrombin 3, increased norepinephrine-induced platelet aggregability.
2. Increased thyroid-binding globulin (TBG) leading to increased circulating total thyroid hormone, as measured by protein-bound iodine (PBI), T4 by column or by radioimmunoassay. Free T3 resin uptake is decreased, reflecting the elevated TBG; free T4 concentration is unaltered.
3. Other binding proteins may be elevated in serum.
4. Sex hormone-binding globulins are increased and result in elevated levels of total circulating sex steroids; however, free or biologically active levels either decrease or remain unchanged.
5. Triglycerides may be increased and levels of various other lipids and lipoproteins may be affected.
6. Glucose tolerance may be decreased.
7. Serum folate levels may be depressed by oral contraceptive therapy. This may be of clinical significance if a woman becomes pregnant shortly after discontinuing NuvaRing®.

12. CARCINOGENESIS, MUTAGENESIS, IMPAIRMENT OF FERTILITY

In a 24-month carcinogenicity study in rats with subdermal implants releasing 10 and 20 mcg etonogestrel per day, (approximately 0.3 and 0.6 times the systemic steady-state exposure of women using NuvaRing®), no drug-related carcinogenic potential was observed. Etonogestrel was not genotoxic in the in vitro Ames/Salmonella reverse mutation assay, the chromosomal aberration assay in Chinese hamster ovary cells or in the in vivo mouse micronucleus test. Fertility returned after withdrawal from treatment (see WARNINGS).

13. PREGNANCY

Pregnancy Category X

(see CONTRAINDICATIONS and WARNINGS).

Teratology studies have been performed in rats and rabbits using the oral route of administration at doses up to 130 and 260 times, respectively, the human NuvaRing® dose (based on body surface area) and have revealed no evidence of harm to the fetus due to etonogestrel.

14. NURSING MOTHERS

The effects of NuvaRing® in nursing mothers have not been evaluated and are unknown. Small amounts of contraceptive steroids have been identified in the milk of nursing mothers and a few adverse effects on the child have been reported, including jaundice and breast enlargement. In addition, contraceptive steroids given in the postpartum period may interfere with lactation by decreasing the quantity and quality of breast milk. Long-term follow-up of children whose mothers used combination hormonal contraceptives while breast-feeding has shown no deleterious effects on infants. However, women who are breast-feeding should be advised not to use NuvaRing® but to use other forms of contraception until the child is weaned.

15. PEDIATRIC USE

Safety and efficacy of NuvaRing® have been established in women of reproductive age. Safety and efficacy are expected to be the same for postpubertal adolescents under the age of 16 and for users 16 years and older. Use of this product before menarche is not indicated.

16. GERIATRIC USE

This product has not been studied in women over 65 years of age and is not indicated in this population.

17. VAGINAL USE

NuvaRing® may not be suitable for women with conditions that make the vagina more susceptible to vaginal irritation or ulceration. Vaginal/cervical erosion or ulceration in women using NuvaRing® has been rarely reported. In some cases, the ring adhered to vaginal tissue, necessitating removal by a healthcare provider.

Some women are aware of the ring at random times during the 21 days of use or during intercourse. During intercourse some sexual partners may feel NuvaRing® in the vagina. However, clinical studies revealed that 90% of couples did not find this to be a problem.

NuvaRing® may interfere with the correct placement and position of a diaphragm. A diaphragm is therefore not recommended as a back-up method with NuvaRing® use.

18. URINARY BLADDER INSERTION

There have been rare reports of inadvertent insertions of NuvaRing® into the urinary bladder, which required cystoscopic removal. Healthcare providers should assess for ring insertion into the urinary bladder in NuvaRing® users who present with persistent urinary symptoms and are unable to locate the ring.

19. EXPULSION

NuvaRing® can be accidentally expelled, for example, while removing a tampon, during intercourse, or with straining during a bowel movement. NuvaRing® should be left in the vagina for a continuous period of three weeks. If the ring is accidentally expelled and is left outside of the vagina for less than three hours contraceptive efficacy is not reduced. NuvaRing® can be rinsed with cool to lukewarm (not hot) water and reinserted as soon as possible, but at the latest within three hours. If NuvaRing® is lost, a new vaginal ring should be inserted and the regimen should be continued without alteration.

If NuvaRing® is out of the vagina for more than three continuous hours

During Weeks 1 and 2

If NuvaRing® has been out of the vagina for more than three continuous hours during the 1st or 2nd week of use, contraceptive efficacy may be reduced. The woman should reinsert the ring as soon as she remembers. A barrier method such as condoms or spermicides must be used until the ring has been used continuously for seven days.

During Week 3

If NuvaRing® has been out of the vagina for more than three continuous hours during the 3rd week of the three-week use period, the woman should discard that ring. One of the following two options should be chosen:

1. Insert a new ring immediately. Inserting a new ring will start the next three-week use period. The woman may not experience a withdrawal bleed from her previous cycle. However, breakthrough spotting or bleeding may occur.
2. Have a withdrawal bleeding and insert a new ring no later than seven days (7×24 hours) from the time the previous ring was removed or expelled. This option should only be chosen if the ring was used continuously for the preceding seven days.

A barrier method such as condoms or spermicides must be used until the new ring has been used continuously for seven days.

20. DISCONNECTED RING

There have been reported cases of NuvaRing® disconnecting at the weld joint. This is not expected to affect the contraceptive effectiveness of NuvaRing®. In the event of a disconnected ring, vaginal discomfort or expulsion (slipping out) is more likely to occur (see EXPULSION). If a woman discovers that her NuvaRing® has disconnected, she should discard the ring and replace it with a new ring.

INFORMATION FOR THE PATIENT

The woman should be instructed regarding the proper use of NuvaRing® (see PATIENT INFORMATION printed below).

ADVERSE REACTIONS

The most common adverse events reported by five to 14% of women using NuvaRing® in clinical trials (n=2501) were the following: vaginitis, headache, upper respiratory tract infection, vaginal secretion, sinusitis, weight gain, and nausea.

The most frequent system-organ class adverse events leading to discontinuation in one to 2.5% of women using NuvaRing® in the trials included the following: device-related events (foreign body sensation, coital problems, device expulsion), vaginal symptoms (discomfort/vaginitis/vaginal secretion), headache, emotional lability, and weight gain.

Listed below are adverse reactions that have been associated with the use of combination hormonal contraceptives. These are also likely to apply to combination vaginal hormonal contraceptives, such as NuvaRing®.

An increased risk of the following serious adverse reactions has been associated with the use of combination hormonal contraceptives (see CONTRAINDICATIONS and WARNINGS):

- Thrombophlebitis and venous thrombosis with or without embolism
- Arterial thromboembolism
- Pulmonary embolism
- Myocardial infarction

- Cerebral hemorrhage
- Cerebral thrombosis
- Hypertension
- Gallbladder disease
- Hepatic adenomas or benign liver tumors

There is evidence of an association between the following conditions and the use of combination hormonal contraceptives:

- Mesenteric thrombosis

- Retinal thrombosis

The following additional adverse reactions have been reported in users of combination hormonal contraceptives and are believed to be drug-related:

- Nausea
- Vomiting
- Gastrointestinal symptoms (such as abdominal pain, cramps and bloating)
- Breakthrough bleeding
- Spotting
- Change in menstrual flow
- Amenorrhea
- Temporary infertility after discontinuation of treatment
- Edema/fluid retention
- Melasma/chloasma which may persist
- Breast changes: tenderness, pain, enlargement, and secretion
- Decrease in serum folate levels
- Exacerbation of porphyria
- Aggravation of varicose veins

- Change in weight or appetite (increase or decrease)
- Change in cervical ectropion and secretion
- Possible diminution in lactation when given immediately postpartum
- Cholestatic jaundice
- Migraine headache
- Rash (allergic)
- Mood changes, including depression
- Vaginitis, including candidiasis
- Change in corneal curvature (steepening)
- Intolerance to contact lenses
- Exacerbation of systemic lupus erythematosus
- Exacerbation of chorea
- Anaphylactic/anaphylactoid reactions, including urticaria, angioedema, and severe reactions with respiratory and circulatory symptoms

The following additional adverse reactions have been reported in users of combination hormonal contraceptives and a causal association has been neither confirmed nor refuted:

- Pre-menstrual syndrome
- Cataracts
- Cystitis-like syndrome
- Headache
- Nervousness
- Dizziness
- Hirsutism
- Loss of scalp hair
- Erythema multiforme
- Dysmenorrhea
- Pancreatitis

- Erythema nodosum
- Hemorrhagic eruption
- Impaired renal function
- Hemolytic uremic syndrome
- Acne
- Changes in libido
- Colitis
- Budd-Chiari Syndrome
- Optic neuritis, which may lead to partial or complete loss of vision

OVERDOSAGE

Overdosage of combination hormonal contraceptives may cause nausea, vomiting, vaginal bleeding, or other menstrual irregularities. Given the nature and design of NuvaRing® it is unlikely that overdosage will occur. If NuvaRing® is broken, it does not release a higher dose of hormones. Serious ill effects have not been reported following acute ingestion of large doses of oral contraceptives by young children. There are no antidotes and further treatment should be symptomatic.

DOSAGE AND ADMINISTRATION

To achieve maximum contraceptive effectiveness, NuvaRing® must be used as directed (see When to Start NuvaRing® below). One NuvaRing® is inserted in the vagina. The ring is to remain in place continuously for three weeks. It is removed for a one-week break, during which a withdrawal bleed usually occurs. A new ring is inserted one week after the last ring was removed.

The user can choose the insertion position that is most comfortable to her, for example, standing with one leg up, squatting, or lying down. The ring is to be compressed and inserted into the vagina. The exact position of NuvaRing® inside the vagina is not critical for its function. The vaginal ring must be inserted on the appropriate day and left in place for three consecutive weeks. This means that the ring is removed three weeks later on the same day of the week as it was inserted and at about the same time. NuvaRing® can be removed by hooking the index finger under the forward rim or by grasping the rim between the index and middle finger and pulling it out. The used ring should be placed in the sachet (foil pouch) and discarded in a waste receptacle out of the reach of children and pets (do not flush in toilet). After a one-week break, during which a withdrawal bleed usually occurs, a new ring is inserted on the same day of the week as it was inserted in the previous cycle. The withdrawal bleed usually starts on day 2–3 after removal of the ring and may not have finished before the next ring is inserted. In order to maintain contraceptive effectiveness, the new ring must be inserted one week after the previous one was removed even if menstrual bleeding has not finished.

When to Start NuvaRing®

IMPORTANT: The possibility of ovulation and conception prior to the first use of NuvaRing® should be considered.

No hormonal contraceptive use in the preceding cycle

Insert NuvaRing® on the first day of the woman's natural cycle (i.e., the first day of her menstrual bleeding). NuvaRing® may also be started on days 2–5 of the woman's cycle, but in this case a barrier method, such as male condoms or spermicide, is recommended for the first seven days of NuvaRing® use in the first cycle.

Changing from a combined hormonal contraceptive

The woman may switch from her previous combined hormonal contraceptive on any day, but at the latest on the day following the usual hormone-free interval, if she has been using her hormonal method consistently and correctly, or if it is reasonably certain that she is not pregnant.

Changing from a progestagen-only method (minipill, implant, or injection) or from a progestagen-releasing intrauterine system (IUS)

The woman may switch on any day from the minipill. She should switch from an implant or the IUS on the day of its removal and from an injectable on the day when the next injection would be due. In all of these cases, the woman should use an additional barrier method such as a male condom or spermicide, for the first seven days.

Following complete first trimester abortion

The woman may start using NuvaRing® within the first five days following a complete first trimester abortion and does not need to use an additional method of contraception. If use of NuvaRing® is not started within five days following a first trimester abortion, the woman should follow the instructions for "No hormonal contraceptive use in the preceding cycle." In the meantime she should be advised to use a non-hormonal contraceptive method.

Following delivery or second trimester abortion

The use of NuvaRing® for contraception may be initiated four weeks postpartum in women who elect not to breast-feed. Women who are breast-feeding should be advised not to use NuvaRing® but to use other forms of contraception until the child is weaned. NuvaRing® use may be initiated four weeks after a second trimester abortion. When NuvaRing® is used postpartum or postabortion, the increased risk of thromboembolic disease must be considered. (See CONTRAINDICATIONS and WARNINGS concerning thromboembolic disease. See PRECAUTIONS for "Nursing Mothers".) If a woman begins using NuvaRing® postpartum, she should be instructed to use an additional method of contraception, such as male condoms or spermicide, for the first seven days. If she has not yet had a period, the possibility of ovulation and conception occurring prior to initiation of NuvaRing® should be considered.

Deviations from the Recommended Regimen

To prevent loss of contraceptive efficacy, women should not deviate from the recommended regimen. NuvaRing® should be left in the vagina for a continuous period of three weeks.

Inadvertent removal, expulsion, or prolonged ring-free interval

If the ring is accidentally expelled and is left outside of the vagina for less than three hours contraceptive efficacy is not reduced. NuvaRing® can be rinsed with cool to lukewarm (not hot) water and reinserted as soon as possible, but at the latest within three hours. If NuvaRing® is lost, a new vaginal ring should be inserted and the regimen should be continued without alteration. If NuvaRing® is out of the vagina for more than three hours, the directions listed under PRECAUTIONS, EXPULSION should be followed.

If the ring-free interval has been extended beyond one week, the possibility of pregnancy should be considered, and an additional method of contraception, such as male condoms or spermicide, MUST be used until NuvaRing® has been used continuously for seven days.

Prolonged Use of NuvaRing®

If NuvaRing® has been left in place for up to one extra week (i.e., up to four weeks total), the woman will remain protected. NuvaRing® should be removed and the woman should insert a new ring after a one-week ring-free interval. The mean serum etonogestrel concentration during the fourth week of continuous use of NuvaRing® was 1272 ± 311 pg/mL compared to a mean concentration range of 1578 ± 408 to 1374 ± 328 pg/mL during weeks one to three. The mean serum ethinyl estradiol concentration during the fourth week of continuous use of NuvaRing® was 16.8 ± 4.6 pg/mL compared to a mean concentration range of 19.1 ± 4.5 to 17.6 ± 4.3 pg/mL during weeks one to three. If NuvaRing® has been left in place for longer than four weeks, pregnancy should be ruled out, and an additional method of contraception, such as male condoms or spermicide, MUST be used until a new NuvaRing® has been used continuously for seven days.

In the event of a missed menstrual period

1. If the woman has not adhered to the prescribed regimen (NuvaRing® has been out of the vagina for more than three hours or the preceding ring-free interval was extended beyond one week) the possibility of pregnancy should be considered at the time of the first missed period and NuvaRing® use should be discontinued if pregnancy is confirmed.
2. If the woman has adhered to the prescribed regimen and misses two consecutive periods, pregnancy should be ruled out.
3. If the woman has retained one NuvaRing® for longer than four weeks, pregnancy should be ruled out.

HOW SUPPLIED

Each NuvaRing® (etonogestrel/ethinyl estradiol vaginal ring) is individually packaged in a reclosable aluminum laminate sachet consisting of three layers, from outside to inside: polyester, aluminum foil, and low-density polyethylene. The ring should be replaced in this reclosable sachet after use for convenient disposal.

Box of 3 sachets | NDC 54868-4832-1

Storage

Prior to dispensing to the user, store refrigerated 2°–8°C (36°–46°F). After dispensing to the user, NuvaRing® can be stored for up to 4 months at 25°C (77°F); excursions permitted to 15°–30°C (59°–86°F) [see USP Controlled Room Temperature]. Avoid storing NuvaRing® in direct sunlight or at temperatures above 30°C (86°F). For the Dispenser: When NuvaRing® is dispensed to the user, place an expiration date on the label. The date should not exceed either 4 months from the date of dispensing or the expiration date, whichever comes first.

Rx only

REFERENCES FURNISHED UPON REQUEST

U.S. Patent No. 5,989,581.

Copyright © 2001, 2010 N.V. Organon, a subsidiary of Merck & Co., Inc. All rights reserved.

34824304T
Rev. 11/10

Additional barcode labeling by:
Physicians Total Care, Inc.
Tulsa, Oklahoma 74146

PATIENT INFORMATION

NUVARING®
(etonogestrel/ethinyl estradiol vaginal ring)
delivers 0.120 mg/0.015 mg per day

PATIENT INFORMATION

Rx only

Read this leaflet carefully before you use NuvaRing® so that you understand the benefits and risks of using this form of birth control. The leaflet gives you information about the possible serious side effects of NuvaRing®. This leaflet will also tell you how to use NuvaRing® properly so that it will give you the best possible protection against pregnancy. Read the information you get whenever you get a new prescription or refill, because there may be new information. This information does not take the place of talking with your healthcare provider.

What is NuvaRing®?

NuvaRing® (NEW-vah-ring) is a flexible combined contraceptive vaginal ring. It is used to prevent pregnancy. It does not protect against HIV infection (AIDS) and other sexually transmitted diseases (STD's) such as chlamydia, genital herpes, genital warts, gonorrhea, hepatitis B, and syphilis.

NuvaRing® contains a combination of a progestin and estrogen, two kinds of female hormones. You insert the ring in your vagina and leave it there for three weeks. After the ring is inserted, it releases a continuous low dose of hormones into your body. You then remove it for a one-week ring-free period.

Contraceptives that contain both an estrogen and a progestin are called combination hormonal contraceptives. Most studies on combination contraceptives have used oral (taken by mouth) contraceptives. NuvaRing® may have the same risks that have been found for combination oral contraceptives. This leaflet will tell you about risks of taking combination oral contraceptives that may also apply to NuvaRing® users. In addition, it will tell you how to use NuvaRing® properly so that it will give you the best possible protection against pregnancy.

Who should not use NuvaRing®?

BOXED WARNING

Cigarette smoking increases the risk of serious cardiovascular side effects when you use combination oral contraceptives. This risk increases even more if you are over age 35 and if you smoke 15 or more cigarettes a day. Women who use combination hormonal contraceptives, including NuvaRing®, are strongly advised not to smoke.

Do not use NuvaRing® if you have any of the following conditions:

- a history of heart attack or stroke
- a history of blood clots in your legs (thrombophlebitis), lungs (pulmonary embolism), or eyes
- a history of blood clots in the deep veins of your legs
- chest pain (angina pectoris)
- severe high blood pressure
- diabetes with complications of the kidneys, eyes, nerves, or blood vessels
- headaches with neurological symptoms
- known or suspected breast cancer or cancer of the lining of the uterus, cervix, or vagina (now or in the past)
- unexplained vaginal bleeding (until a diagnosis is reached by your healthcare provider)
- yellowing of the whites of the eyes or of the skin (jaundice) during pregnancy or during previous use of hormonal birth control of any kind (the pill, patch, vaginal ring, injection, or implant)
- liver tumor (benign or cancerous)
- heart valve or heart rhythm disorders that may be associated with formation of blood clots
- need for a long period of bed rest following major surgery
- known or suspected pregnancy
- active liver disease with abnormal liver function tests
- an allergy or hypersensitivity to any of the components of NuvaRing®

Tell your healthcare provider if you have ever had any of the conditions just listed. Your healthcare provider can suggest another method of birth control.

Talk with your healthcare provider about using NuvaRing® if you:

- smoke
- recently had a baby
- recently had a miscarriage or abortion
- are breast-feeding
- are taking other medications

In addition, talk to your healthcare provider about using NuvaRing® if you have any of the following conditions. Women with any of these conditions should be checked often by their doctor or healthcare provider if they choose to use NuvaRing®.

- a family history of breast cancer
- breast nodules, fibrocystic disease, an abnormal breast x-ray, or abnormal mammogram
- diabetes
- elevated cholesterol or triglycerides
- high blood pressure
- migraine or other headaches or epilepsy
- depression
- gallbladder, liver, heart, or kidney disease
- scanty or irregular menstrual periods
- plan to have major surgery (You may need to stop using NuvaRing® for a while to reduce your chance of getting blood clots.)
- any condition that makes the vagina get irritated easily
- prolapsed (dropped) uterus, dropped bladder (cystocele), or rectal prolapse (rectocele)
- severe constipation
- history of toxic shock syndrome

How should I use NuvaRing®?

For the best protection from pregnancy, use NuvaRing® exactly as directed. Insert one NuvaRing® in the vagina and keep it in place for three weeks in a row. Remove it for a one-week break and then insert a new ring. During the one-week break, you will usually have your menstrual period. Your healthcare provider should examine you at least once a year to see if there are any signs of side effects of NuvaRing® use.

When should I start NuvaRing®?

Follow the instructions in one of the sections below to find out when to start using NuvaRing®:

If you did not use a hormonal contraceptive in the preceding cycle

Insert NuvaRing® on the first day of your cycle, (i.e., the first day of menstrual bleeding). NuvaRing® will work immediately, it is not necessary to use an additional contraceptive method. You may also start on days 2–5 of your cycle, but in this case make sure you also use an extra method of birth control (barrier method), such as male condoms or spermicide for the first seven days of NuvaRing® use in the first cycle.

If you are changing from a combined hormonal contraceptive pill or patch (containing both progestin and estrogen)

Switch from your previous combined hormonal contraceptive on any day, but at the latest on the day following the usual hormone-free interval by inserting NuvaRing®. If you have been using your hormonal contraceptive method consistently and correctly, no extra birth control method should be needed.

If you are changing from a progestagen-only method (minipill, implant or injection) or from a progestagen-releasing intrauterine system (IUS)

You may switch on any day from a minipill. You should switch from an implant or the IUS on the day of its removal and from an injectable on the day when the next injection would be due. In all of these cases, you should use an extra method of birth control, such as a male condom or spermicide, for the first seven days of ring use.

Following first trimester abortion or miscarriage

If you start using NuvaRing® within five days after a complete first trimester abortion or miscarriage, you do not need to use an extra method of contraception.
If NuvaRing® is not started within five days after a first trimester abortion or miscarriage, begin NuvaRing® at the time of your next menstrual period. Counting the first day of your menstrual period as "Day 1", insert NuvaRing® on or before Day 5 of the cycle, even if you have not finished bleeding. During this first cycle, use an extra method of birth control, such as male condoms or spermicide, for the first seven days of ring use.

How do I insert NuvaRing®?

1. Each NuvaRing® comes in a reclosable foil pouch. After washing and drying your hands, remove NuvaRing® from its foil pouch. Keep the foil pouch for proper disposal of the ring after use. Choose the position that is most comfortable for you. For example, lying down, squatting, or standing with one leg up (Figures 1a, 1b, and 1c, respectively).

Figures 1a, 1b, and 1c. Positions for NuvaRing® insertion.

2. Hold NuvaRing® between your thumb and index finger (Figure 2a) and press the opposite sides of the ring together (Figure 2b).

Figures 2a and 2b. Holding NuvaRing® and pressing the sides together.

3. Gently push the folded ring into your vagina (Figures 3a and 3b). The exact position of NuvaRing® in the vagina is not important for it to work (Figures 3c and 3d).

Figures 3a, 3b, 3c, and 3d. Inserting and positioning of NuvaRing®.

Although some women may be aware of NuvaRing® in the vagina, most women do not feel it once it is in place. If you feel discomfort, NuvaRing® is probably not inserted back far enough in the vagina. Use your finger to gently push the NuvaRing® farther into your vagina. There is no danger of NuvaRing® being pushed too far up in the vagina or getting lost. NuvaRing® can be inserted only as far as the end of the vagina, where the cervix (the narrow, lower end of the uterus) will block NuvaRing® from going any farther.

4. Once inserted, keep NuvaRing® in place for three weeks in a row.

How do I remove NuvaRing®?

Figure 4. Removing NuvaRing®.

1. Remove the ring three weeks after insertion on the same day of the week as it was inserted, at about the same time of day.
You can remove NuvaRing® by hooking the index finger under the forward rim or by holding the rim between the index and middle finger and pulling it out (Figure 4).
2. Place the used ring in the foil pouch and properly dispose of it in a waste receptacle out of the reach of children and pets. Do not throw it in the toilet.
Your menstrual period will usually start two to three days after the ring is removed and may not have finished before the next ring is inserted. To continue to have pregnancy protection, you must insert the new ring one week after the last one was removed, even if your menstrual period has not stopped.

If you locate the ring in your vagina, but are unable to remove it, please contact your healthcare provider.

When do I insert a new ring?

After no more than a one-week ring-free break, insert a new ring on the same day of the week as it was removed in the last cycle. If the ring-free interval has been extended beyond one week, the possibility of pregnancy should be considered, and an extra method of birth control, such as male condoms or spermicide, MUST be used until NuvaRing® has been used continuously for seven days.

If NuvaRing® slips out:

NuvaRing® can accidentally slip out of the vagina while removing a tampon, during intercourse, or straining during a bowel movement. If NuvaRing® slips out of the vagina and it has been out for less than three hours, you should still be protected from pregnancy. NuvaRing® can be rinsed with cool to lukewarm (not hot) water and reinserted as soon as possible, and at the latest within three hours of removal or expulsion (slipping out).

If NuvaRing® is out of the vagina for more than three continuous hours:

During Weeks 1 and 2: If the ring has been out of the vagina for more than three continuous hours during the 1st or 2nd week of use, contraceptive effectiveness may be reduced. Reinsert ring as soon as you remember and use an extra method of birth control, such as male condoms or spermicide, until the ring has been used continuously for seven days.

During Week 3: If NuvaRing® slips out of the vagina for more than three continuous hours during the 3rd week of the three-week use period, throw the ring away and choose one of the following two options.

1. Insert a new ring immediately. Inserting a new ring will start the next three-week use period. You may not experience a period from your previous cycle. However, breakthrough spotting or bleeding may occur.
2. Have your period and insert a new ring no later than seven days (7×24 hours) from the time the previous ring was removed or expelled. This option should only be chosen if the ring was used continuously for the preceding seven days.

In addition, a barrier method such as condoms or spermicides must be used until the ring has been used continuously for seven days.

Women with conditions affecting the vagina, such as a prolapsed (dropped) uterus, may be more likely to have NuvaRing® slip out of the vagina. If NuvaRing® slips out repeatedly, you should consult with your healthcare provider.

If NuvaRing® is in your vagina too long:

If NuvaRing® has been left in your vagina for an extra week or less (four weeks total or less), you will remain protected. Remove NuvaRing® and insert a new ring after a one-week ring-free break.

If NuvaRing® has been left in place for more than four weeks, you may not be adequately protected from pregnancy and you must check to be sure you are not pregnant. You MUST use an extra method of birth control, such as male condoms or spermicide, until the new NuvaRing® has been in place for seven days in a row.

If you miss a menstrual period:

You must check to be sure that you are not pregnant if:

1. you miss a period and NuvaRing® was out of the vagina for more than three hours during the three weeks of ring use
2. you miss a period and waited longer than one week to insert a new ring
3. you have followed the instructions and you miss two periods in a row
4. you have left NuvaRing® in place for longer than four weeks

Can I use tampons when using NuvaRing®?

Use of tampons will not reduce the contraceptive efficacy of NuvaRing®. Insert NuvaRing® before inserting a tampon. You should pay particular attention when removing a tampon to be sure that the ring is not accidentally pulled out. If this should occur, simply rinse the ring in cool to lukewarm (not hot) water and immediately reinsert it.

Can I use vaginal medications?

Use of spermicides or vaginal yeast products will not reduce the contraceptive efficacy of NuvaRing®.

What should I do if my NuvaRing® disconnects?

There have been reported cases of NuvaRing® disconnecting at the weld joint causing the ring to change shape and straighten out. This is not expected to affect the contraceptive effectiveness of NuvaRing®. If NuvaRing® disconnects, expulsion (slipping out) is more likely to occur (see "If NuvaRing® slips out"). If you discover the ring has disconnected, you should discard the ring and replace it with a new ring.

Overdose

NuvaRing® is unlikely to cause an overdose because the ring holding the medicine releases a steady amount of contraceptive hormones. Do not use more than one ring at a time. Overdose of combination hormonal contraceptives may cause nausea, vomiting, or vaginal bleeding.

What should I avoid while using NuvaRing®?

Cigarette smoking increases the risk of serious cardiovascular side effects when you use combination oral contraceptives, including NuvaRing®. This risk increases even more if you are over age 35 and if you smoke 15 or more cigarettes a day. Women who use combination hormonal contraceptives, like NuvaRing®, are strongly advised not to smoke.

Do not breast-feed while using NuvaRing®. Some of the medicine may pass through the milk to the baby and could cause yellowing of the skin (jaundice) and breast enlargement in your baby. NuvaRing® could also decrease the amount and quality of your breast milk.

The hormones in NuvaRing® can interact with many other medicines and herbal supplements. Tell your healthcare provider about any medicines you are taking, including prescription medicines, over-the-counter medicines, herbal remedies, and vitamins.

The blood levels of the hormones released by NuvaRing® were increased when women used a vaginal medication (miconazole nitrate) for a yeast infection while NuvaRing® was in place. The pregnancy protection of NuvaRing® is not likely to be changed by use of these products. The blood levels of these hormones were not changed when women used vaginal, water-based spermicides (nonoxynol or N-9 products) along with NuvaRing®.

Certain drugs and herbal supplements may interact with combined hormonal contraceptives to make them less effective in preventing pregnancy or cause an increase in breakthrough bleeding. Such drugs include rifampin, drugs used for epilepsy such as barbiturates (for example, phenobarbital), carbamazepine, and phenytoin, primidone, topiramate, phenylbutazone, modafinil, and some drugs used for HIV such as ritonavir. Pregnancies and breakthrough bleeding have been reported by users of combined hormonal contraceptives who also used the herbal supplement St. John's Wort. You may need to use a non-hormonal method of contraception during any cycle in which you take drugs that can make oral contraceptives less effective. Be sure to tell your healthcare provider if you are taking or start taking any other medications, including non-prescription products or herbal products while using NuvaRing®.

While using NuvaRing®, you should not rely upon a diaphragm when you need a back-up method of birth control because NuvaRing® may interfere with the correct placement and position of a diaphragm.

If you are scheduled for any laboratory tests, tell your doctor or healthcare provider you are using NuvaRing®. Contraceptive hormones may change certain blood tests results.

What are the possible risks and side effects of NuvaRing®?

- Blood clots
  The hormones in NuvaRing® may cause changes in your blood clotting system which may allow your blood to clot more easily. If blood clots form in your legs, they can travel to the lungs and cause a sudden blockage of a vessel carrying blood to the lungs. Rarely, clots occur in the blood vessels of the eye and may cause blindness, double vision, or other vision problems. The risk of getting blood clots may be greater with the type of progestin in NuvaRing® than with some other progestins in certain low-dose birth control pills. It is unknown if the risk of blood clots is different with NuvaRing® use than with the use of certain birth control pills.
  If you take hormonal contraceptives and need elective surgery, need to stay in bed for a prolonged illness or have recently delivered a baby, you may be at risk of developing blood clots. You should consult your doctor or healthcare provider about stopping hormonal contraceptives three to four weeks before surgery and not taking hormonal contraceptives for two weeks after surgery or during bed rest. You should also not take hormonal contraceptives soon after delivery of a baby. It is advisable to wait for at least four weeks after delivery if you are not breast-feeding. If you are breast-feeding, you should wait until you have weaned your child before using the pill (see PRECAUTIONS, NURSING MOTHERS).
- Strokes and heart attacks
  Hormonal contraceptives may increase your risk of strokes (blockage of blood flow to the brain) or heart attacks (blockage of blood flow to the heart). Any of these conditions can cause death or serious disability. Smoking greatly increases the risk of having strokes and heart attacks. Furthermore, smoking and the use of combination hormonal contraceptives, like NuvaRing®, greatly increases the chances of developing and dying of heart disease. If you use combination hormonal contraceptives, including NuvaRing®, you should not smoke.
- High blood pressure and heart disease
  Combination hormonal contraceptives, including NuvaRing®, can worsen conditions like high blood pressure, diabetes, and problems with cholesterol and triglycerides.
- Cancer of the reproductive organs and breast
  Breast cancer has been diagnosed slightly more often in women who use the pill than in women of the same age who do not use the pill. This small increase in the number of breast cancer diagnoses gradually disappears during the 10 years after stopping use of the pill. It is not known whether the difference is caused by the pill. It may be that women taking the pill are examined more often, so that breast cancer is more likely to be detected. You should have regular breast examinations by a healthcare provider and examine your own breasts monthly. Tell your healthcare provider if you have a family history of breast cancer or if you have had breast nodules or an abnormal mammogram.
  Women who currently have or have had breast cancer should not use hormonal contraceptives, including NuvaRing®, because breast cancer is usually a hormone-sensitive tumor.
  Some studies have found an increase in the incidence of cancer of the cervix in women who use oral contraceptives. However, this finding may be related to factors other than the use of oral contraceptives. There is insufficient evidence to rule out the possibility that pills may cause such cancers.
- Gallbladder disease
  Combination hormonal contraceptive users may have a higher chance of having gallbladder disease.
- Liver tumors
  In rare cases, combination hormonal contraceptives, like NuvaRing®, can cause non-cancerous (benign) but dangerous liver tumors. These benign liver tumors can break and cause fatal internal bleeding. In addition, it is possible that women who use combination hormonal contraceptives, like NuvaRing®, have a higher chance of getting liver cancer. However, liver cancers are extremely rare.
- Lipid metabolism and inflammation of the pancreas
  In women with inherited defects of lipid metabolism, there have been reports of significant elevations of plasma triglycerides during estrogen therapy. This has led to pancreatitis in some cases.

The common side effects reported by NuvaRing® users are:

- vaginal infections and irritation
- vaginal secretion
- headache
- weight gain
- nausea

In addition to the risks and side effects listed above, users of combination hormonal contraceptives have reported the following side effects:

- vomiting
- change in appetite
- abdominal cramps and bloating
- breast tenderness or enlargement
- irregular vaginal bleeding or spotting
- changes in menstrual cycle
- temporary infertility after treatment
- fluid retention (edema)
- spotty darkening of the skin, particularly on the face
- rash
- weight changes
- depression
- intolerance to contact lenses
- nervousness
- dizziness
- loss of scalp hair

Call your healthcare provider right away if you get any of the symptoms listed below. They may be signs of a serious problem:

- sharp chest pain, coughing blood, or sudden shortness of breath (possible clot in the lung)
- pain in the calf (back of lower leg; possible clot in the leg)
- crushing chest pain or heaviness in the chest (possible heart attack)
- sudden severe headache or vomiting, dizziness or fainting, problems with vision or speech, weakness, or numbness in an arm or leg (possible stroke)
- sudden partial or complete loss of vision (possible clot in the eye)
- yellowing of the skin or whites of the eyes (jaundice), especially with fever, tiredness, loss of appetite, dark colored urine, or light colored bowel movements (possible liver problems)
- severe pain, swelling, or tenderness in the abdomen (gallbladder or liver problems)
- sudden fever (usually 102°F or more), vomiting, diarrhea, dizziness, fainting, or a sunburn-like rash on the face or body (very rarely, toxic shock syndrome)
- breast lumps (possible breast cancer or benign breast disease)
- irregular vaginal bleeding or spotting that happens in more than one menstrual cycle or lasts for more than a few days
- urgent, frequent, burning and/or painful urination, and cannot locate the ring in the vagina (rarely, accidental placement of NuvaRing® into the urinary bladder)
- swelling (edema) of your fingers or ankles
- difficulty in sleeping, weakness, lack of energy, fatigue, or a change in mood (possible severe depression)

How effective is NuvaRing®?

If NuvaRing® is used according to the directions, your chance of getting pregnant is about 1 to 2% a year. This means that, for every 100 women who use NuvaRing® for a year, one or two will become pregnant. Your chance of getting pregnant increases if NuvaRing® is not used exactly according to the directions.

By comparison, the chances of getting pregnant in the first year of typical use (not always following directions exactly) of other methods of birth control are as follows:

No birth control method: | 85%
Spermicides alone: | 26%
Periodic abstinence methods
(calendar, ovulation, thermometer): | 25%
Withdrawal: | 19%
Cervical Cap with spermicides: | 20 to 40%
Vaginal sponge: | 20 to 40%
Diaphragm with spermicides: | 20%
Condom alone (male): | 14%
Condom alone (female): | 21%
Oral contraceptives: | 5%
IUD: | less than 1 to 2%
Implants: | less than 1%
Injection: | less than 1%
Sterilization: | less than 1%

Other Information

- Store NuvaRing® at room temperature, 25°C (77°F). Temperatures can be from 15°-30°C (59°-86°F). Avoid direct sunlight or storing above 30°C (86°F).
- Medicines are sometimes prescribed for conditions that are not mentioned in patient information leaflets. Do not use NuvaRing® for a condition for which it was not prescribed. Do not give NuvaRing® to anyone else who may want to use it.
- Place the used ring in the reclosable foil pouch and properly dispose of it in a waste receptacle out of the reach of children and pets.

This leaflet summarizes the most important information about NuvaRing®. If you would like more information, talk with your healthcare provider. You can ask your pharmacist or healthcare provider for information about NuvaRing® that is written for health professionals.

1-877-NUVARING

U.S. Patent No. 5,989,581.

Copyright © 2001, 2010 N.V. Organon, a subsidiary of Merck & Co., Inc. All rights reserved.

34823804T
Rev. 11/10

PRINCIPAL DISPLAY PANEL - 3 Ring Carton

For the Dispenser: Store refrigerated 2°-8°C (36°-46°F).

NDC 54868-4832-1

NUVARING®
(etonogestrel/ethinyl estradiol vaginal ring)
delivers 0.120 mg/0.015 mg per day

For Vaginal Use

Keep out of the reach of children.

This product is intended to prevent
pregnancy. It does not protect against
HIV infection (AIDS) and other sexually
transmitted diseases.

Rx only

Contains 3 Rings